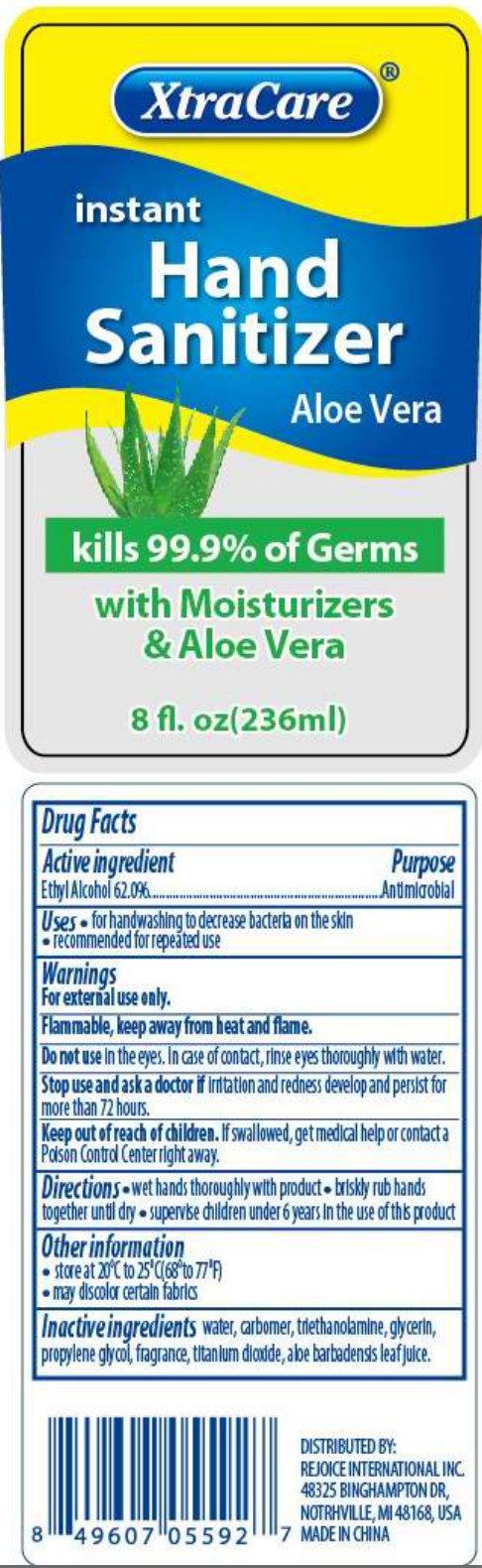 DRUG LABEL: XtraCare instant Hand Sanitizer Aloe Vera
                
NDC: 57337-002 | Form: LIQUID
Manufacturer: Rejoice International
Category: otc | Type: HUMAN OTC DRUG LABEL
Date: 20130228

ACTIVE INGREDIENTS: ALCOHOL 62 mL/100 mL
INACTIVE INGREDIENTS: WATER; TROLAMINE; GLYCERIN; PROPYLENE GLYCOL; TITANIUM DIOXIDE; ALOE VERA LEAF

XtraCare instant Hand Sanitizer Aloe Vera

Active ingredient

Ethyl Alcohol 62.0%

Purpose

Antimicrobial

Uses

- for handwashing to decrease bacteria on the skin
- recommended for repeated use

Warnings

For external use only.
Flammable, keep away from heat and flame.

Do not use

In the eyes. In case of contact, rinse eyes thoroughly with water.

Stop use and ask a doctor if

irritation and redness develop and persist for more than 72 hours.

Keep out of reach of children.

If swallowed, get medical help or contact a Poison Control Center right away.

Directions

- wet hands thoroughly with product
- briskly rub hands together until dry
- supervise children under 6 years in the use of this product

Other information

- store at 20^0C to 25^0C (68^0F to 77^0F)
- may discolor certain fabrics

Inactive ingredients

water, carbomer, triethanolamine, glycerin, propylene glycol, fragrance, titanium dioxide, aloe barbadensis leaf juice.

XtraCare

DISTRIBUTED BY: REJOICE INTERNATIONAL INC. 48325 BINGHAMPTON DR, NOTRHVILLE, MI 48168, USA
MADE IN CHINA.

PACKAGE LABEL

XtraCare instant Hand Sanitizer Aloe Vera kills 99.9% of Germs with Moisturizers and Aloe Vera 8 fl. oz(236ml)